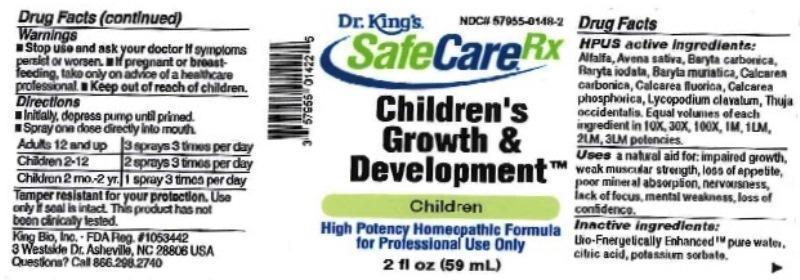 DRUG LABEL: Childrens Growth and Development
NDC: 57955-0148 | Form: LIQUID
Manufacturer: King Bio, Inc.
Category: homeopathic | Type: HUMAN OTC DRUG LABEL
Date: 20170308

ACTIVE INGREDIENTS: ALFALFA 10 [hp_X]/59 mL; AVENA SATIVA FLOWERING TOP 10 [hp_X]/59 mL; BARIUM CARBONATE 10 [hp_X]/59 mL; BARIUM IODIDE 10 [hp_X]/59 mL; BARIUM CHLORIDE DIHYDRATE 10 [hp_X]/59 mL; OYSTER SHELL CALCIUM CARBONATE, CRUDE 10 [hp_X]/59 mL; CALCIUM FLUORIDE 10 [hp_X]/59 mL; TRIBASIC CALCIUM PHOSPHATE 10 [hp_X]/59 mL; LYCOPODIUM CLAVATUM SPORE 10 [hp_X]/59 mL; THUJA OCCIDENTALIS LEAFY TWIG 10 [hp_X]/59 mL
INACTIVE INGREDIENTS: WATER; ANHYDROUS CITRIC ACID; POTASSIUM SORBATE

Childrens Growth & Development™

ACTIVE INGREDIENT

HPUS active ingredients: Alfalfa, Avena sativa, Baryta carbonica, Baryta iodata, Baryta muriatica, Calcarea carbonica, Calcarea fluorica, Calcarea phosphorica, Lycopodium clavatum, Thuja occidentalis. Equal volumes of each ingredient in 10X, 30X, 100X, 1M, 1LM, 2LM, 3LM potencies.

INDICATIONS AND USAGE

Uses a natural aid for: impaired growth, weak muscular strength, loss of appetite, poor mineral absorption, nervousness, lack of focus, mental weakness, loss of confidence.

INACTIVE INGREDIENT

Inactive ingredients: Bio-Energetically Enhanced™ pure water, citric acid, potassium sorbate.

Warnings

- Stop use and ask your doctor if symptoms persist or worsen.
- If pregnant or breastfeeding, take only on advice of a healthcare professional.

- Keep out of reach of children.

Directions

- Initially, depress pump until primed.
- Spray one dose directly into mouth.
- Adults 12 and up: 3 sprays 3 times per day.
- Children 2-12: 2 sprays 3 times per day.
- Children 2 mo.-2 yr.: 1 spray 3 times per day.

OTHER SAFETY INFORMATION

Tamper resistant for your protection. Use only if seal is intact. This product has not been clinically tested.

PURPOSE

Uses a natural aid for:

- impaired growth
- weak muscular strength
- loss of appetite
- poor mineral absorption
- nervousness
- lack of focus
- mental weakness
- loss of confidence